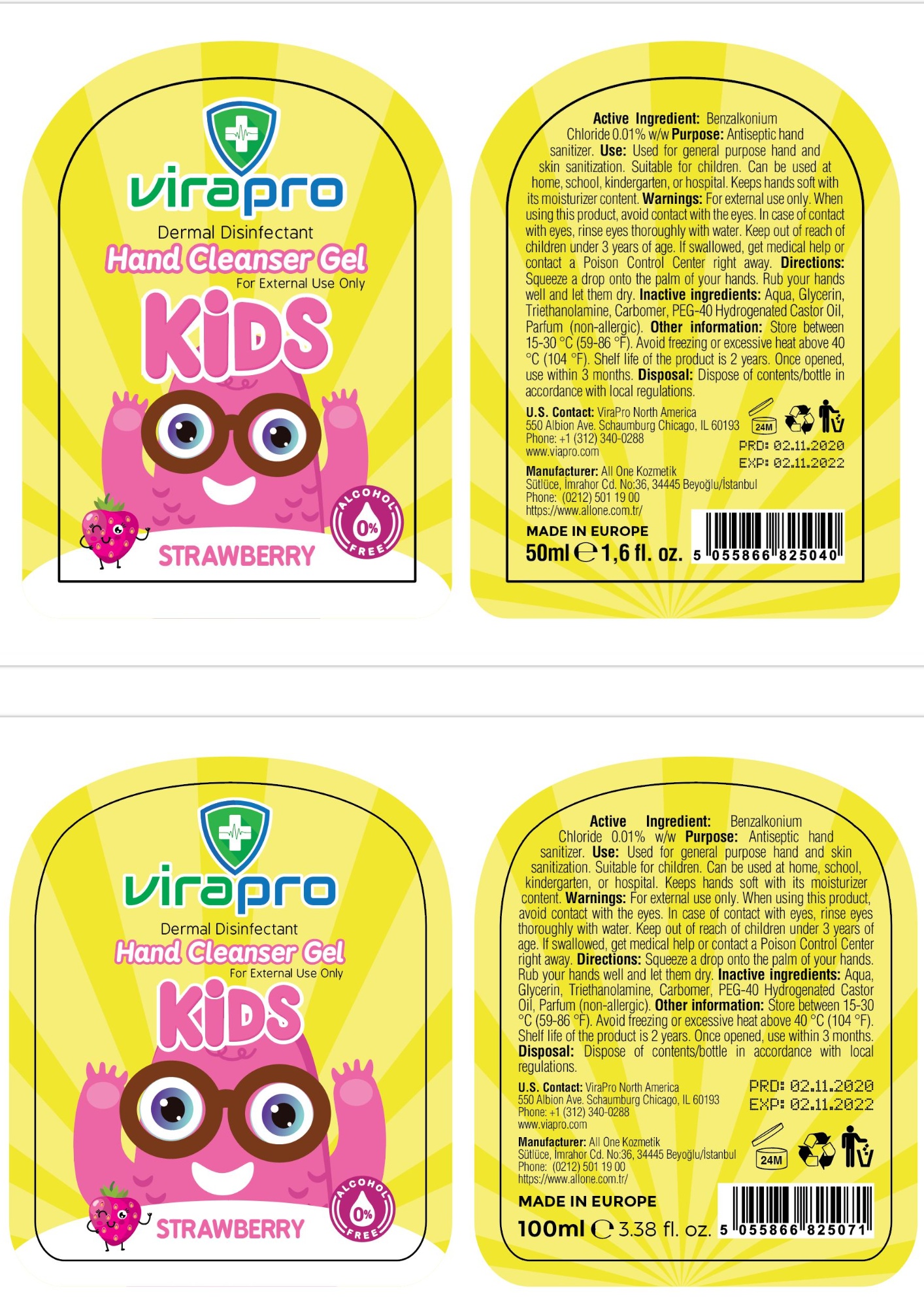 DRUG LABEL: VIRAPRO KIDS HANDS CLEANSER
NDC: 75348-003 | Form: GEL
Manufacturer: ALL ONE KOZMETIK SANAYI DIS TICARET ANONIM SIRKETI
Category: otc | Type: HUMAN OTC DRUG LABEL
Date: 20201021

ACTIVE INGREDIENTS: BENZALKONIUM CHLORIDE 0.01 mg/100 mL
INACTIVE INGREDIENTS: GLYCERIN; CARBOMER 980; WATER; POLYOXYL 40 HYDROGENATED CASTOR OIL; TROLAMINE

Hand Sanitizer Strawberry

Active Ingredient(s)

Benzalkonium Chloride 0.01% w/w

Purpose

Antiseptic Hand Sanitizer

Use

Used for general purpose hand and skin sanitization. Suitable for children. Can be used at home, school, kindergarten, or hospital. Keeps hands soft with its moisturizer content.

Warnings

For external use only.

When using this product, avoid contact with the eyes. In case of contact with eyes, rinse eyes thoroughly with water.

Keep out of reach of children under 3 years of age. If swallowed, get medical help or contact a Poison Control Center right away.

Directions

Squeeze a drop onto the palm of your hands. Rub your hands well and let them dry.

Inactive ingredients

Aqua, Glycerin, Triethanolamine, Carbomer, PEG-40 Hydrogenated Castor Oil, Parfum (non-allergic)

Other information

Store between 15-30 °C (59-86 °F). Avoid freezing or excessive heat above 40 °C (104 °F).

Shelf life of the product is 2 years. Once opened, use within 3 months.

DISPOSAL AND WASTE HANDLING

Dispose of contents/bottle in accordance with local regulations.

Package Label - Principal Display Panel

virapro

Dermal Disinfectant

Hand Cleanser Gel

For External Use Only

KIDS

STRAWBERRY

ALCOHOL FREE 0%

U.S. Contact: ViraPro North America

550 Albion Ave. Schaumburg Chicago, IL 60193

Phone: +1 (312) 340-0288

www.viapro.com

Manufacturer: All One Kozmetik

Sutluce, Imrahor Cd. No:36, 34445 Beyoglu/Istanbul

Phone: (0212) 501 19 00

https://www.allone.com.tr/

MADE IN EUROPE